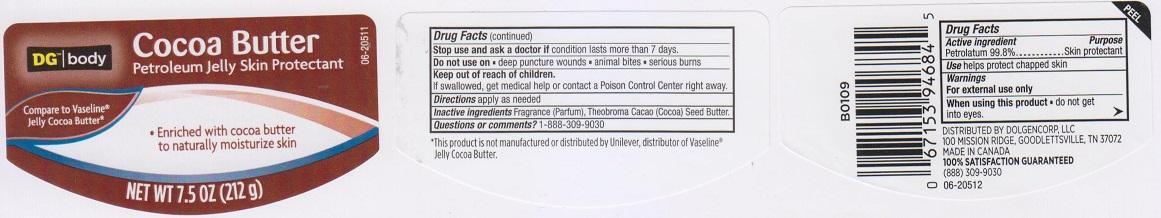 DRUG LABEL: DG BODY
NDC: 55910-317 | Form: JELLY
Manufacturer: DOLGENCORP INC
Category: otc | Type: HUMAN OTC DRUG LABEL
Date: 20150810

ACTIVE INGREDIENTS: PETROLATUM 99.8 g/100 g
INACTIVE INGREDIENTS: COCOA BUTTER

DRUG FACTS

Active ingredient

Petrolatum 99.8%

Purpose

Skin protectant

Uses

helps protect chapped skin

Warnings

For external use only

When using this product

do not get into eyes

Stop use and ask a doctor if

condition lasts more than 7 days

Do not use on

- deep puncture wounds
- animal bites
- serious burns

Keep out of reach of children.

If swallowed, get medical help or contact a Poison Control Center right away.

Directions

apply as needed

Inactive ingredients

Fragrance (Parfum), Theobroma Cacao (Cocoa) Seed Butter

Qeustions or comments?

1-888-309-9030